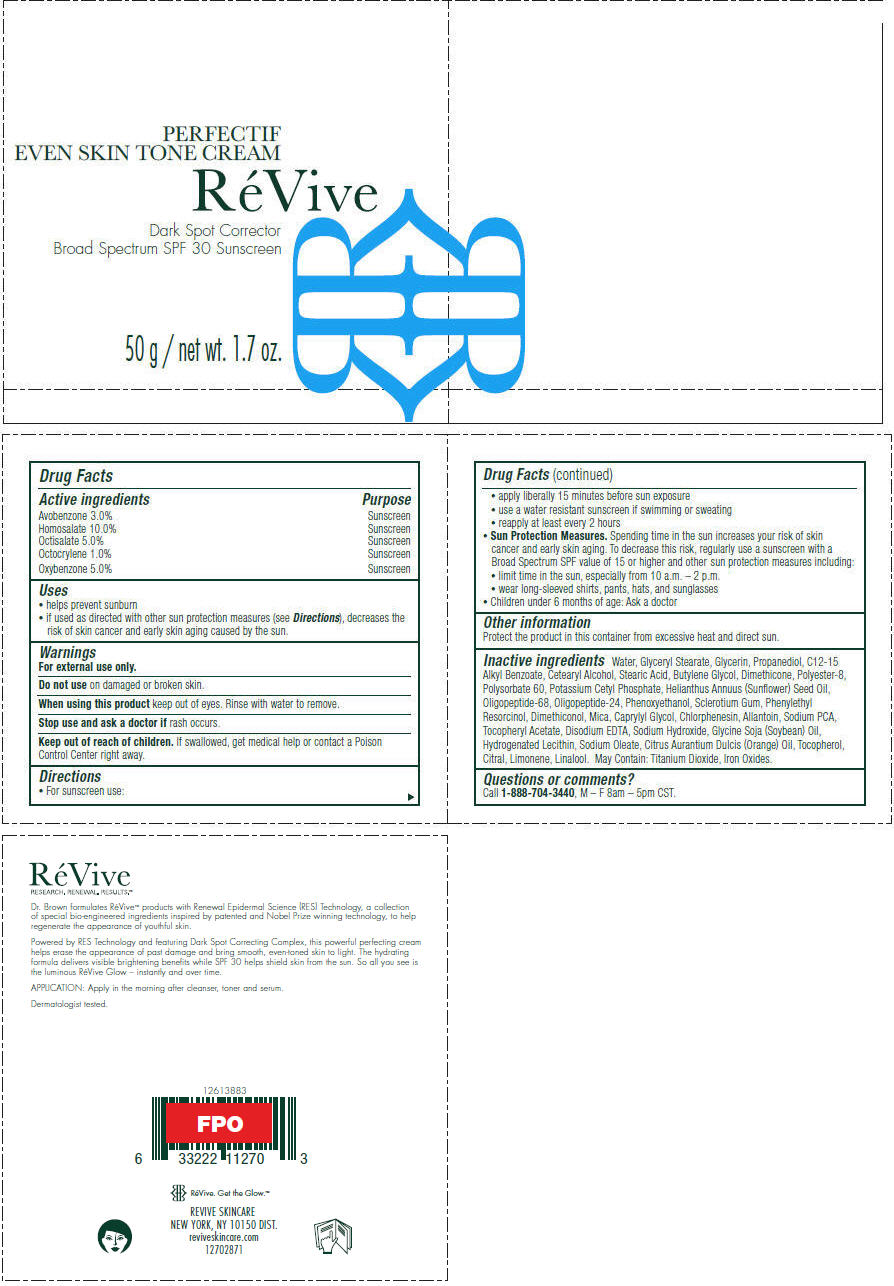 DRUG LABEL: ReVive Perfectif Even Skin Tone 
NDC: 58411-417 | Form: CREAM
Manufacturer: RéVive Skincare
Category: otc | Type: HUMAN OTC DRUG LABEL
Date: 20180122

ACTIVE INGREDIENTS: AVOBENZONE 30 mg/1 g; HOMOSALATE 100 mg/1 g; OCTISALATE 50 mg/1 g; OCTOCRYLENE 10 mg/1 g; OXYBENZONE 50 mg/1 g
INACTIVE INGREDIENTS: WATER; GLYCERYL MONOSTEARATE; GLYCERIN; PROPANEDIOL; ALKYL (C12-15) BENZOATE; CETOSTEARYL ALCOHOL; STEARIC ACID; BUTYLENE GLYCOL; DIMETHICONE; POLYESTER-8 (1400 MW, CYANODIPHENYLPROPENOYL CAPPED); POLYSORBATE 60; POTASSIUM CETYL PHOSPHATE; SUNFLOWER OIL; PHENOXYETHANOL; BETASIZOFIRAN; PHENYLETHYL RESORCINOL; MICA; CAPRYLYL GLYCOL; CHLORPHENESIN; ALLANTOIN; SODIUM PYRROLIDONE CARBOXYLATE; .ALPHA.-TOCOPHEROL ACETATE; EDETATE DISODIUM ANHYDROUS; SODIUM HYDROXIDE; SOYBEAN OIL; HYDROGENATED SOYBEAN LECITHIN; SODIUM OLEATE; ORANGE OIL; TOCOPHEROL; CITRAL; LIMONENE, (+)-; LINALOOL, (+/-)-; TITANIUM DIOXIDE; FERROUS OXIDE

RéVive Perfectif Even Skin Tone
Cream Dark Spot Corrector Broad Spectrum SPF 30 Sunscreen

Drug Facts

ACTIVE INGREDIENT

Active ingredients | Purpose
Avobenzone 3.0% | Sunscreen
Homosalate 10.0% | Sunscreen
Octisalate 5.0% | Sunscreen
Octocrylene 1.0% | Sunscreen
Oxybenzone 5.0% | Sunscreen

Uses

- helps prevent sunburn
- if used as directed with other sun protection measures (see Directions), decreases the risk of skin cancer and early skin aging caused by the sun.

Warnings

For external use only.

Do not use on damaged or broken skin.

When using this product keep out of eyes. Rinse with water to remove.

Stop use and ask a doctor if rash occurs.

Keep out of reach of children. If swallowed, get medical help or contact a Poison Control Center right away.

Directions

- For sunscreen use:
  - apply liberally 15 minutes before sun exposure
  - use a water resistant sunscreen if swimming or sweating
  - reapply at least every 2 hours
- Sun Protection Measures. Spending time in the sun increases your risk of skin cancer and early skin aging. To decrease this risk, regularly use a sunscreen with a Broad Spectrum SPF value of 15 or higher and other sun protection measures including:
  - limit time in the sun, especially from 10 a.m. – 2 p.m.
  - wear long-sleeved shirts, pants, hats, and sunglasses
- Children under 6 months of age: Ask a doctor

Other information

Protect the product in this container from excessive heat and direct sun.

Inactive ingredients

Water, Glyceryl Stearate, Glycerin, Propanediol, C12-15 Alkyl Benzoate, Cetearyl Alcohol, Stearic Acid, Butylene Glycol, Dimethicone, Polyester-8, Polysorbate 60, Potassium Cetyl Phosphate, Helianthus Annuus (Sunflower) Seed Oil, Oligopeptide-68, Oligopeptide-24, Phenoxyethanol, Sclerotium Gum, Phenylethyl Resorcinol, Dimethiconol, Mica, Caprylyl Glycol, Chlorphenesin, Allantoin, Sodium PCA, Tocopheryl Acetate, Disodium EDTA, Sodium Hydroxide, Glycine Soja (Soybean) Oil, Hydrogenated Lecithin, Sodium Oleate, Citrus Aurantium Dulcis (Orange) Oil, Tocopherol, Citral, Limonene, Linalool. May Contain: Titanium Dioxide, Iron Oxides.

Questions or comments?

Call 1-888-704-3440, M – F 8am – 5pm CST.

PRINCIPAL DISPLAY PANEL - 50 g Jar Carton

PERFECTIF
EVEN SKIN TONE CREAM

RéVive

Dark Spot Corrector
Broad Spectrum SPF 30 Sunscreen

50 g / net wt. 1.7 oz.